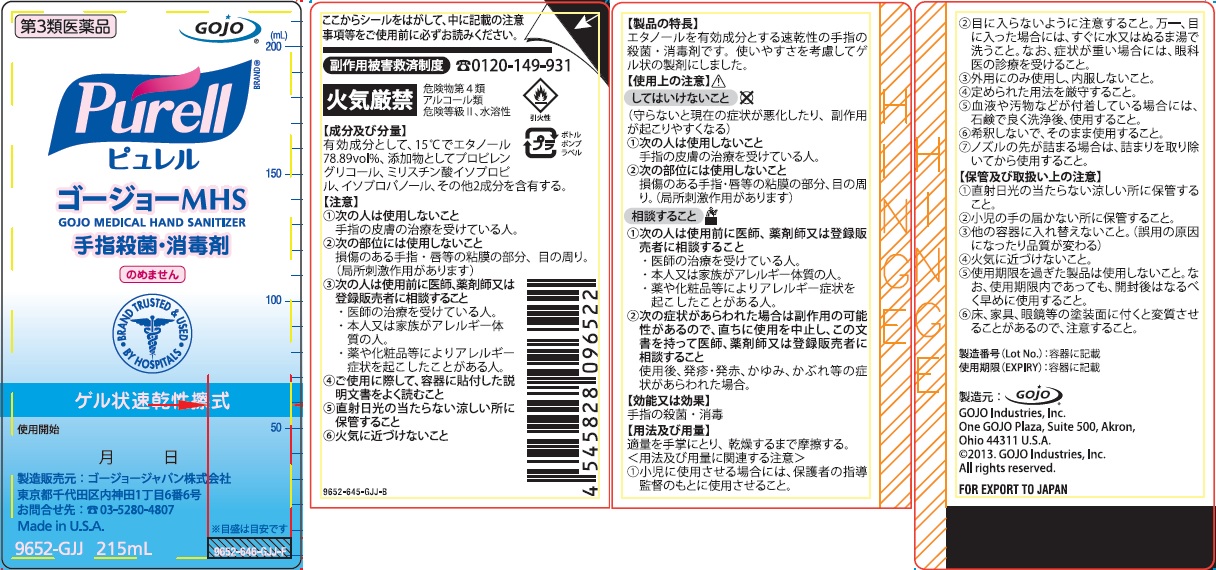 DRUG LABEL: GOJO Medical Hand Sanitizer
NDC: 21749-660 | Form: GEL
Manufacturer: GOJO Industries, Inc.
Category: otc | Type: HUMAN OTC DRUG LABEL
Date: 20241231

ACTIVE INGREDIENTS: ALCOHOL 0.8 mL/1 mL
INACTIVE INGREDIENTS: WATER; ISOPROPYL ALCOHOL; ISOPROPYL MYRISTATE; PROPYLENE GLYCOL; CARBOMER INTERPOLYMER TYPE A (ALLYL SUCROSE CROSSLINKED); AMINOMETHYLPROPANOL

GOJO Medical Hand Sanitizer